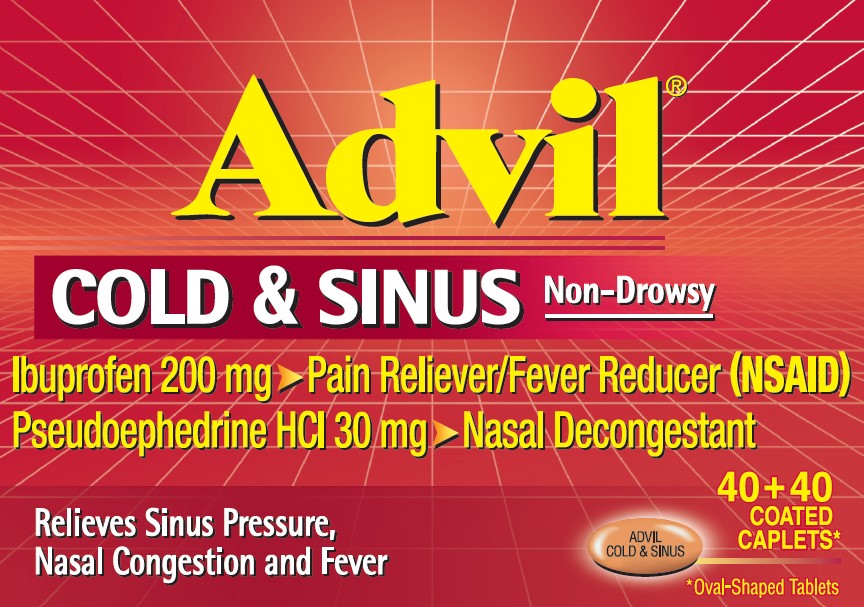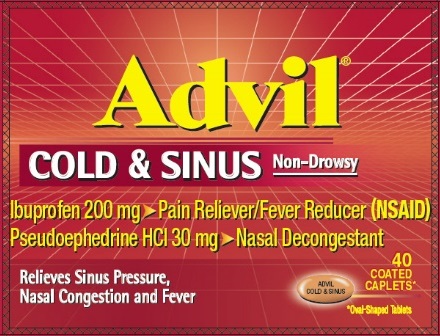 DRUG LABEL: ADVIL COLD AND SINUS
NDC: 0573-0180 | Form: TABLET, COATED
Manufacturer: Haleon US Holdings LLC
Category: otc | Type: HUMAN OTC DRUG LABEL
Date: 20250613

ACTIVE INGREDIENTS: IBUPROFEN 200 mg/1 1; PSEUDOEPHEDRINE HYDROCHLORIDE 30 mg/1 1
INACTIVE INGREDIENTS: DIACETYLATED MONOGLYCERIDES; CARNAUBA WAX; SILICON DIOXIDE; STARCH, CORN; CROSCARMELLOSE SODIUM; METHYLPARABEN; MICROCRYSTALLINE CELLULOSE; SHELLAC; POVIDONE, UNSPECIFIED; PROPYLPARABEN; SODIUM BENZOATE; SODIUM LAURYL SULFATE; STEARIC ACID; SUCROSE; FERRIC OXIDE RED; TITANIUM DIOXIDE

Drug Facts

ACTIVE INGREDIENTS (IN EACH CAPLET)

Ibuprofen 200 mg (NSAID)*

Pseudoephedrine HCl 30 mg

*nonsteroidal anti-inflammatory drug

PURPOSES

Pain reliever/fever reducer

Nasal decongestant

USES

temporarily relieves these symptoms associated with the common cold or flu:

- headache
- fever
- sinus pressure
- nasal congestion
- minor body aches and pains

WARNINGS

Allergy alert:

Ibuprofen may cause a severe allergic reaction, especially in people allergic to aspirin. Symptoms may include:

- hives
- facial swelling
- asthma (wheezing)
- shock
- skin reddening
- rash
- blisters

If an allergic reaction occurs, stop use and seek medical help right away.

Stomach bleeding warning:

This product contains an NSAID, which may cause severe stomach bleeding. The chance is higher if you:

- are age 60 or older
- have had stomach ulcers or bleeding problems
- take a blood thinning (anticoagulant) or steroid drug
- take other drugs containing prescription or nonprescription NSAIDs [aspirin, ibuprofen, naproxen, or others]
- have 3 or more alcoholic drinks every day while using this product
- take more or for a longer time than directed

Heart attack and stroke warning

NSAIDs, except aspirin, increase the risk of heart attack, heart failure, and stroke. These can be fatal. The risk is higher if you use more than directed or for longer than directed.

Do not use

- in children under 12 years of age
- if you have ever had an allergic reaction to any other pain reliever/fever reducer
- right before or after heart surgery
- if you are now taking a prescription monoamine oxidase inhibitor (MAOI) (certain drugs for depression, psychiatric, or emotional conditions, or Parkinson's disease), or for 2 weeks after stopping the MAOI drug. If you do not know if your prescription drug contains an MAOI, ask a doctor or pharmacist before taking this product.

Ask a doctor before use if

- stomach bleeding warning applies to you
- you have problems or serious side effects from taking pain relievers or fever reducers
- you have a history of stomach problems, such as heartburn
- you have high blood pressure, heart disease, liver cirrhosis, kidney disease, asthma, thyroid disease, diabetes, have trouble urinating due to an enlarged prostate gland, or had a stroke
- you are taking a diuretic

Ask a doctor or pharmacist before use if you are

- under a doctor's care for any serious condition
- taking any other product that contains pseudoephedrine or any other nasal decongestant
- taking aspirin for heart attack or stroke, because ibuprofen may decrease this benefit of aspirin
- taking any other drug

When using this product

- take with food or milk if stomach upset occurs

Stop use and ask a doctor if

- you experience any of the following signs of stomach bleeding:
  - feel faint
  - vomit blood
  - have bloody or black stools
  - have stomach pain that does not get better
- you have symptoms of heart problems or stroke:
  - chest pain
  - trouble breathing
  - weakness in one part or side of body
  - slurred speech
  - leg swelling
- fever gets worse or lasts more than 3 days
- nasal congestion lasts for more than 7 days
- symptoms continue or get worse
- redness or swelling is present in the painful area
- you get nervous, dizzy, or sleepless
- any new symptoms appear

If pregnant or breast-feeding,

ask a health professional before use. It is especially important not to use ibuprofen during the last 3 months of pregnancy unless definitely directed to do so by a doctor because it may cause problems in the unborn child or complications during delivery.

Keep out of reach of children.

In case of overdose, get medical help or contact a Poison Control Center right away.

DIRECTIONS

- do not take more than directed
- the smallest effective dose should be used
- adults and children 12 years of age and over:
  - take 1 caplet every 4 to 6 hours while symptoms persist. If symptoms do not respond to 1 caplet, 2 caplets may be used.
  - do not use more than 6 caplets in any 24-hour period unless directed by a doctor
- children under 12 years of age: do not use

OTHER INFORMATION

- store at 20-25°C (68-77°F). Avoid excessive heat above 40°C (104°F).
- read all warnings and directions before use. Keep carton.

INACTIVE INGREDIENTS

acetylated monoglycerides, carnauba wax, colloidal silicon dioxide, corn starch, croscarmellose sodium, methylparaben, microcrystalline cellulose, pharmaceutical glaze, pharmaceutical ink, povidone, pregelatinized starch, propylparaben, sodium benzoate, sodium lauryl sulfate, stearic acid, sucrose, synthetic iron oxides, titanium dioxide

QUESTIONS OR COMMENTS?

Call toll free 1-800-88-ADVIL

Additional information – 40 + 40 ct.

Product inside sealed in plastic blister with foil backing. Do Not Use if plastic blister or foil barrier is broken.

PRINCIPAL DISPLAY PANEL

Advil®

COLD & SINUS Non-Drowsy

Ibuprofen 200 mg ‣ Pain Reliever/Fever Reducer (NSAID)

Pseudoephedrine HCl 30 mg ‣ Nasal Decongestant

Relieves Sinus Pressure,
Nasal Congestion and Fever

40
COATED
CAPLETS*

*Oval-Shaped Tablets

Principal Display Panel – 40 + 40 ct.

Advil ®

COLD & SINUSNon-Drowsy

Ibuprofen 200 mg ‣ Pain Reliever/Fever Reducer (NSAID)

Pseudoephedrine HCl 30 mg ‣ Nasal Decongestant

Relieves Sinus Pressure,
Nasal Congestion and Fever

40 + 40
COATED
CAPLETS*

*Oval-Shaped Tablets